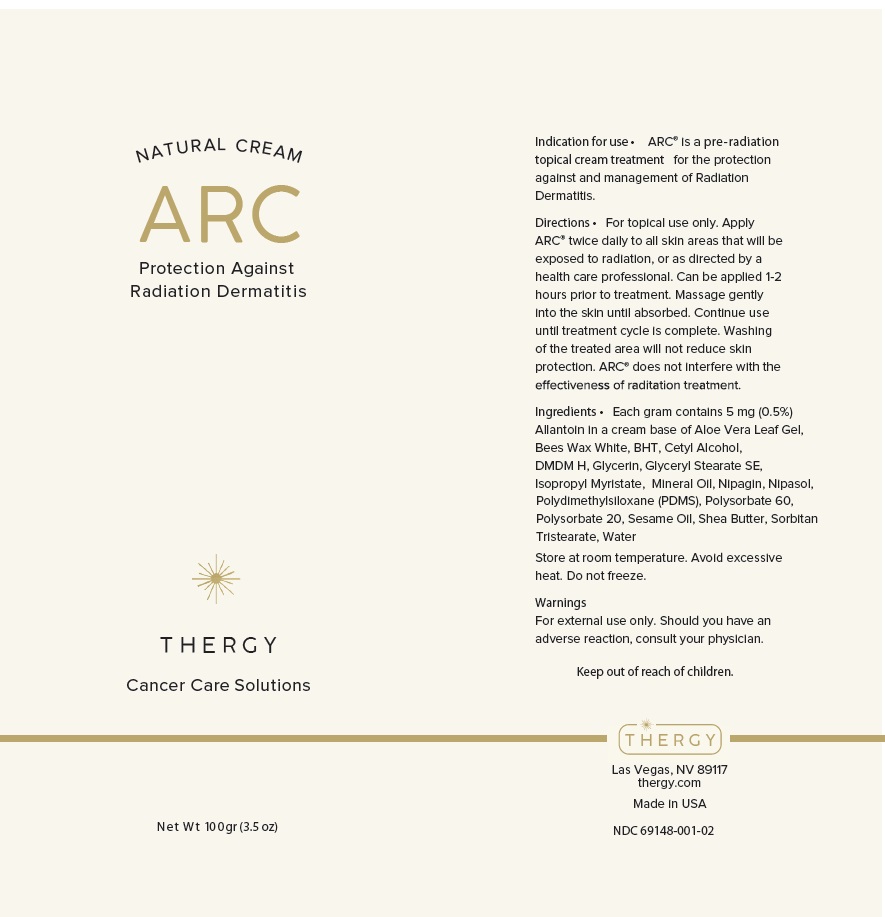 DRUG LABEL: ARC Skin Protectant
NDC: 69148-001 | Form: OINTMENT
Manufacturer: Anjon Biologics, Inc
Category: otc | Type: HUMAN OTC DRUG LABEL
Date: 20240418

ACTIVE INGREDIENTS: ALLANTOIN 0.5 g/100 g
INACTIVE INGREDIENTS: ALOE VERA LEAF; WHITE WAX; BUTYLATED HYDROXYTOLUENE; CETYL ALCOHOL; DMDM HYDANTOIN; GLYCERIN; GLYCERYL STEARATE SE; ISOPROPYL MYRISTATE; MINERAL OIL; METHYLPARABEN SODIUM; PROPYLPARABEN; DIMETHICONE; POLYSORBATE 60; POLYSORBATE 20; SESAME OIL; SHEA BUTTER; SORBITAN TRISTEARATE; WATER

NATURAL CREAM ARC

PURPOSE

Protection Against Radiation Dermatitis

Indication for use •

ARC® is a pre-radiation topical cream treatment for the protection against and management of Radiation Dermatitis.

Directions •

For topical use only. Apply ARC® twice daily to all skin areas that will be exposed to radiation, or as directed by a health care professional. Can be applied 1-2 hours prior to treatment. Massage gently into the skin until absorbed. Continue use until treatment cycle is complete. Washing of the treated area will not reduce skin protection. ARC® does not interfere with the effectiveness of radiation treatment.

Ingredients •

Each gram contains 5 mg (0.5%) Allantoin in a cream base of

INACTIVE INGREDIENT

Aloe Vera Leaf Gel, Bees Wax White, BHT, Cetyl Alcohol, DMDM H, Glycerin, Glyceryl Stearate SE, Isopropyl Myristate, Mineral Oil, Nipagin, Nipasol, Polydimethylsiloxane (PDMS), Polysorbate 60, Polysorbate 20, Sesame Oil, Shea Butter, Sorbitan Tristearate, Water

OTHER SAFETY INFORMATION

Store at room temperature. Avoid excessive heat. Do not freeze.

Warnings

For external use only. Should you have an adverse reaction, consult your physician.

Keep out of reach of children.

NATURAL CREAM

THERGY

Cancer Care Solutions

Las Vegas, NV 89117
thergy.com

Made in USA